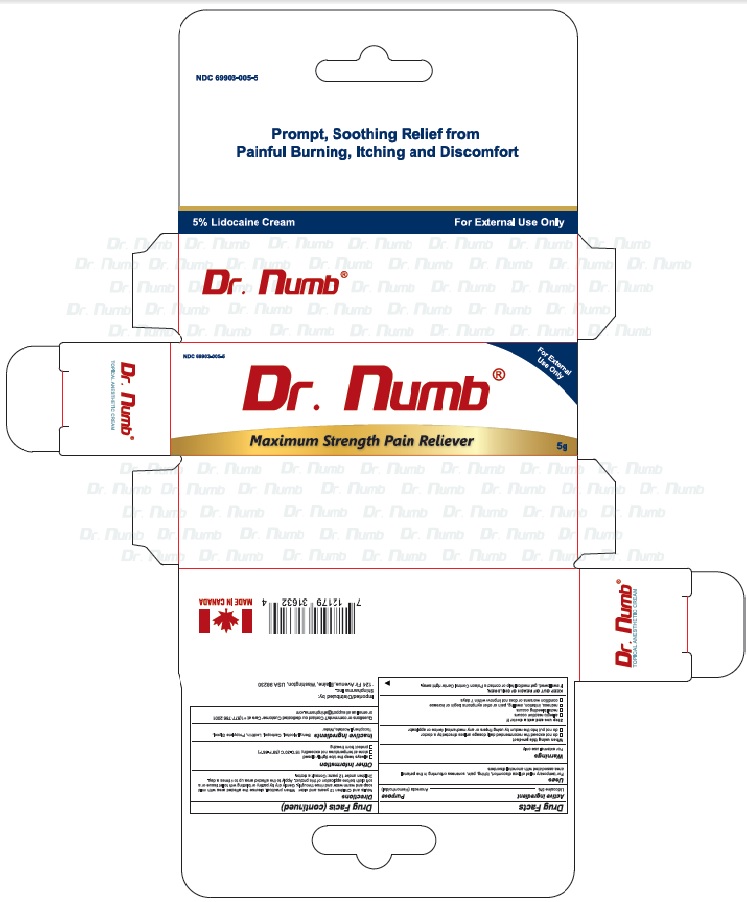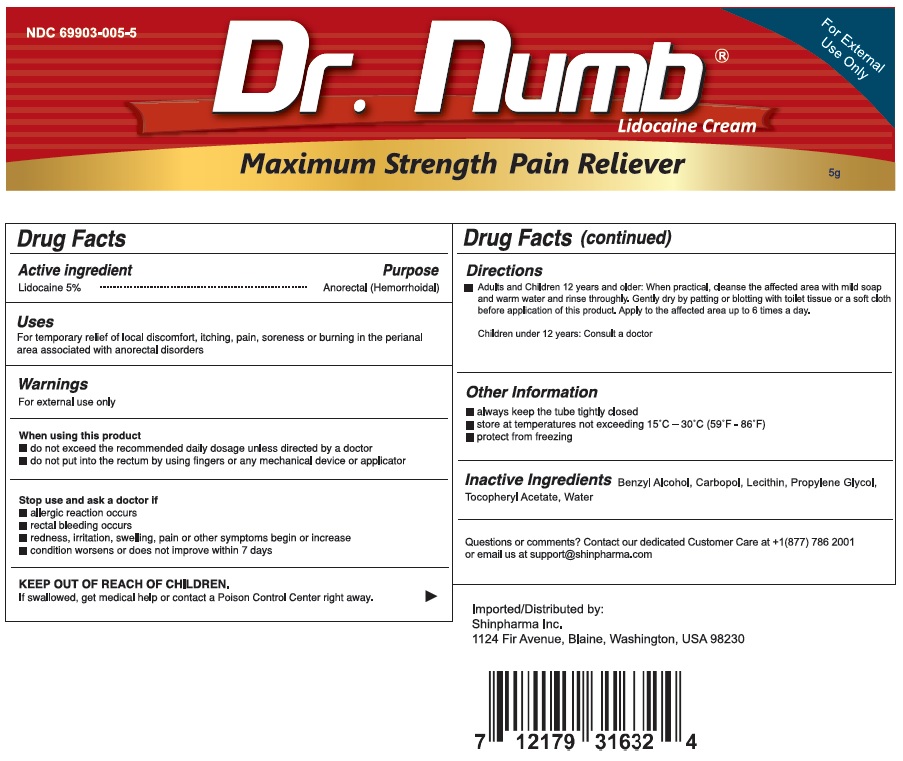 DRUG LABEL: Lidocaine
NDC: 69903-005 | Form: CREAM
Manufacturer: Shinpharma Inc
Category: otc | Type: HUMAN OTC DRUG LABEL
Date: 20240403

ACTIVE INGREDIENTS: LIDOCAINE 5 g/100 g
INACTIVE INGREDIENTS: WATER; CARBOMER HOMOPOLYMER, UNSPECIFIED TYPE; LECITHIN, SUNFLOWER; PROPYLENE GLYCOL; ALPHA-TOCOPHEROL ACETATE; BENZYL ALCOHOL

Dr. Numb Maximum Strength Pain Reliever

Active ingredient

Lidocaine 5%

Purpose

Anorectal (Hemorrhoidal)

Uses

For temporary relief of local discomfort, itching, soreness or burning in the perianal area associated with anorectal disorders

Warnings

For external use only

When using this product

- do not exceed the recommended daily dosage unless directed by a doctor
- do not put into the rectum by using fingers or any mechanical device or applicator

Stop use and ask a doctor if

- allergic reaction occurs
- rectal bleeding occurs
- redness, irritattion, swelling, pain or other symptoms begin or increase
- condition worsens or does not improve within 7 days

Keep Out Of Reach Of Children

If swallowed, get medical help or contact a Poison Control Center right away.

Directions

Adults and Children 12 years and older: When practical, cleanse the affected area with mild soap and warm water and rinse thoroughly. Gently dry by patting or blotting with toilet tissue or a soft cloth before application of this product. Apply to the affected area up to 6 times a day. Children under 12 years: Consult a doctor.

Other Information

- always keep the tube tightly closed
- store at temperatures not exceeding 15°C - 30°C (59°F - 86°F)
- protect from freezing

Inactive Ingredients

Benzyl Alcohol, Carbopol, Lecithin, Propylene Glycol, Tocopheryl Acetate, Water

Questions or comments?

Contact our dedicated Customer Care at +1(877)786 2001 or email us at support@shinpharma.com

Principal Display Panel

Dr. Numb

Maximum Strength Pain Reliever

Prompt, Soothing Relief from Painful Burning, Itching and Discomfort